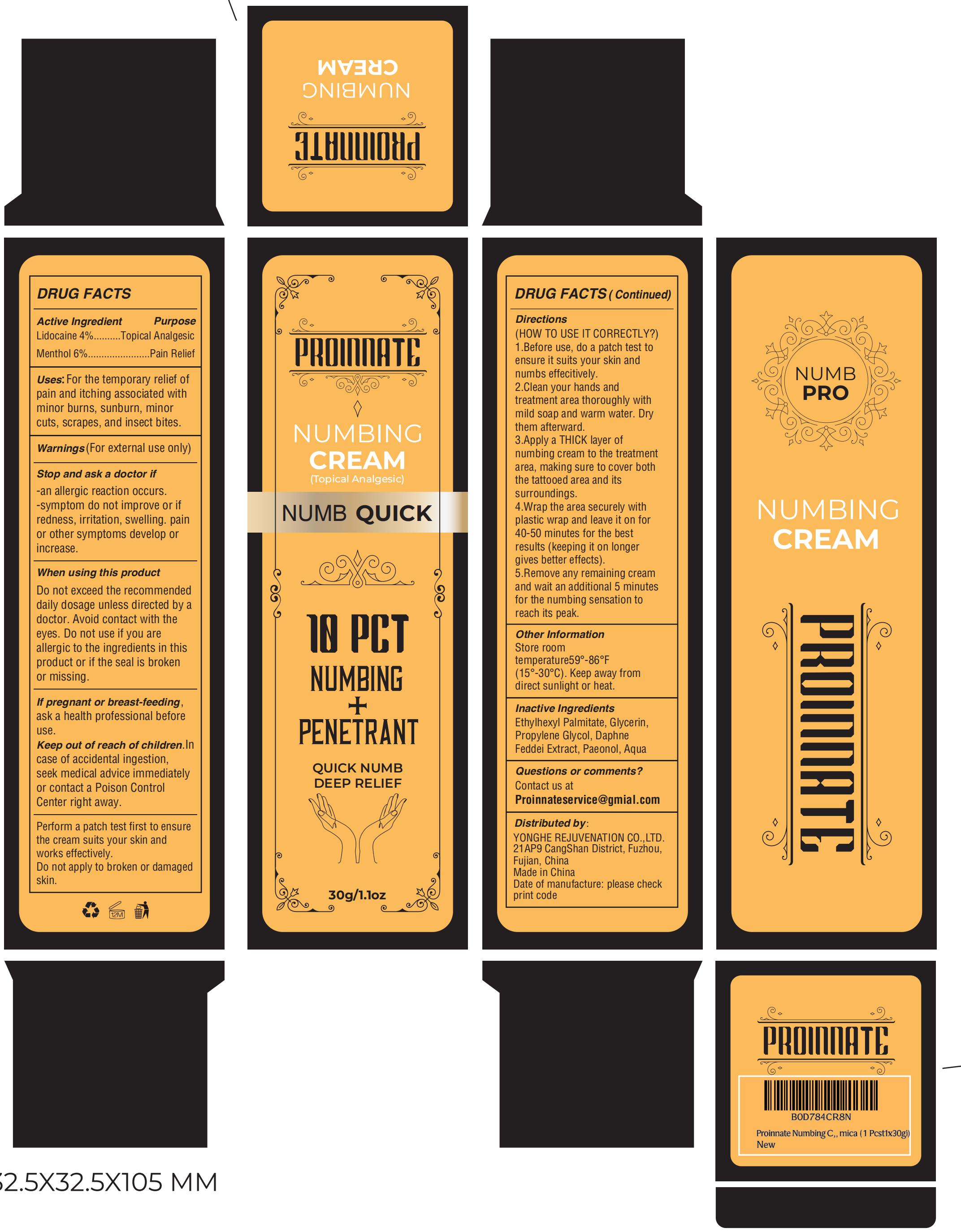 DRUG LABEL: PROINNATE Numbing Cream
NDC: 83566-562 | Form: CREAM
Manufacturer: Guangdong Aimu Biological Technology Co., Ltd
Category: otc | Type: HUMAN OTC DRUG LABEL
Date: 20251222

ACTIVE INGREDIENTS: LIDOCAINE 4 g/100 g; MENTHOL 6 g/100 g
INACTIVE INGREDIENTS: AQUA; PAEONOL; ETHYLHEXYL PALMITATE; GLYCERIN; PROPYLENE GLYCOL; DAPHNE ODORA ROOT

PROINNATE Numbing Cream

Active Ingredients

Lidocaine 4%
Menthol 6%

Purpose

For the temporary relief of pain and itching associated with minor burns, sunburn, minorcuts, scrapes, and insect bites.

Uses

1.Before use, do a patch test toensure it suits your skin andnumbs effecitively.
2.Clean your hands andtreatment area thoroughly withmild soap and warm water. Drythem afterward.
3.Apply a THICK layer ofnumbing cream to the treatmentarea, making sure to cover boththe tattooed area and itssurroundings.

4.Wrap the area securely withplastic wrap and leave it on for40-50 minutes for the bestresults (keeping it on longergives better effects).

5.Remove any remaining creamand wait an additional 5 minutes for the numbing sensation toreach its peak.

Warnings

For extemal use only

Stop Use

Stop and ask a doctor if-an allergic reaction occurs.-symptom do not improve or ifredness, irritation, swelling. painor other symptoms develop orincrease.

Do Not Use

Do not exceed the recommendeddaily dosage unless directed by adoctor. Avoid contact with theeyes. Do not use if you areallergic to the ingredients in thisproduct or if the seal is brokenor missing

When Using

If pregnant or breast-feeding,ask a health professional beforeuse.

Keep Out Of Reach Of Children

Keep out ofreach of children. incase of accidental ingestion,seek medical advice immediatelyor contact a Poison ControlCenter right away.

Inactive ingredients

Ethylhexyl Palmitate 12%
Glycerin 5%
Propylene Glycol 5%
Daphne Feddei Extract 0.5%
Aqua 67%
Paeonol 0.5%

Dosage & administration

Apply a THiCK layer ofnumbing cream to the treatmentarea, making sure to cover boththe tattooed area and its surroundings